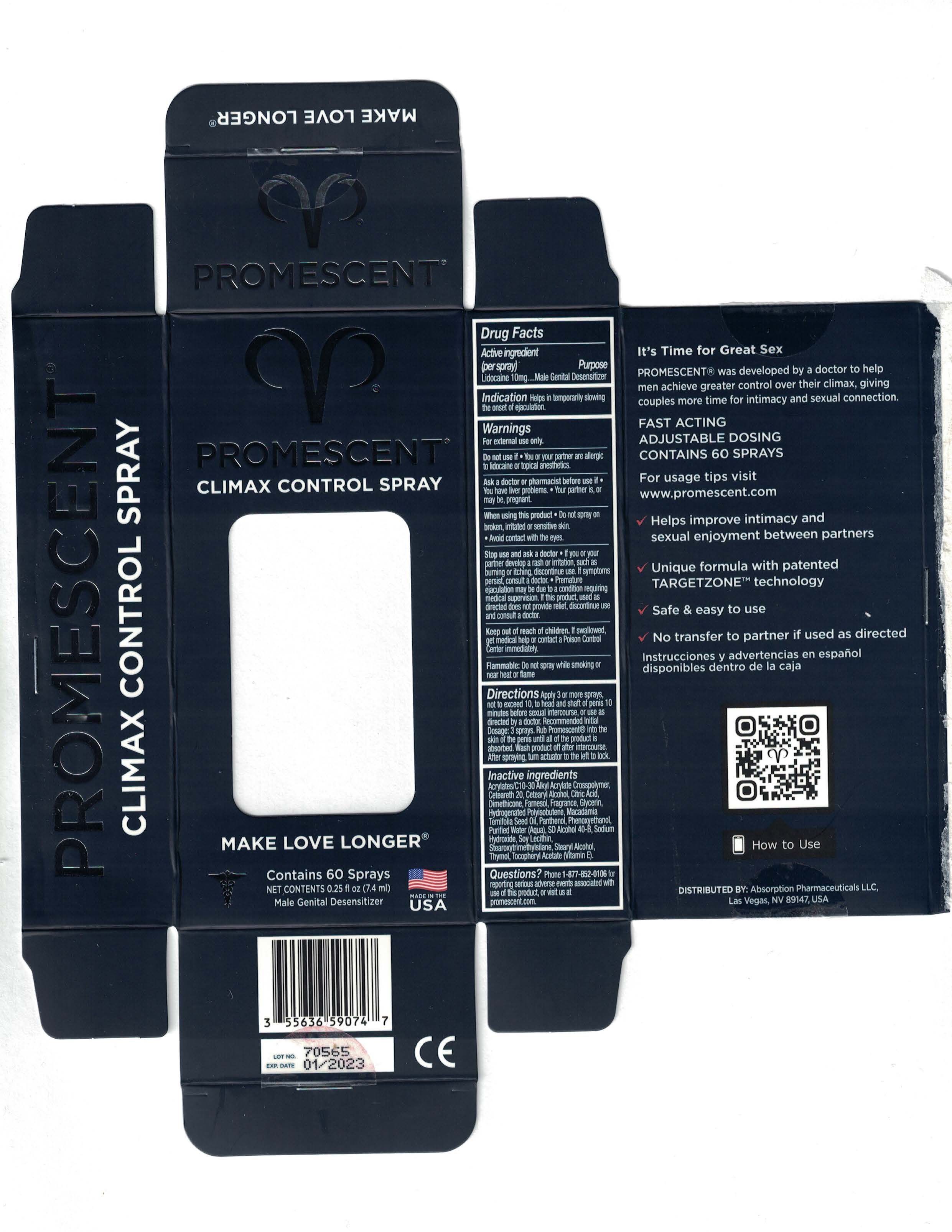 DRUG LABEL: Promescent
NDC: 55636-590 | Form: SPRAY
Manufacturer: Absorption
Category: otc | Type: HUMAN OTC DRUG LABEL
Date: 20260209

ACTIVE INGREDIENTS: LIDOCAINE 10 g/100 g
INACTIVE INGREDIENTS: WATER; CARBOMER INTERPOLYMER TYPE A (ALLYL SUCROSE CROSSLINKED); GLYCERIN; PANTHENOL; CITRIC ACID MONOHYDRATE; POLYOXYL 20 CETOSTEARYL ETHER; CETOSTEARYL ALCOHOL; DIMETHICONE; HYDROGENATED POLYBUTENE (1300 MW); STEAROXYTRIMETHYLSILANE; STEARYL ALCOHOL; MACADAMIA OIL; .ALPHA.-TOCOPHEROL ACETATE; LECITHIN, SOYBEAN; FARNESOL; THYMOL; ALCOHOL; PHENOXYETHANOL; SODIUM HYDROXIDE

Promescent

Active Ingredient (per spray)

Lidocaine approx. 10mg

Purpose

Anesthetic

Keep out of reach of children

If swallowed, get medical help or contact a Poison Control Center right away

Use:

Helps in temporarily slowing the onset of ejaculation.

Warnings:

For external use only.

Do not use if

- You or your partner are allergic to lidocaine or topical anesthetics.
- Your partner is, or may be pregnant.

Ask a doctor or pharmacist before use if

- You have liver problems.

When using this product

- Do not spray on broken, irritated or sensitive skin.
- Avoid contact with the eyes.

Stop use and ask a doctor

- If you or your partner develop a rash or irritation, such as burning or itching, dicontinue use. If symptoms persist, consult a doctor.
- Premature ejaculation may be due to a condition requiring medical supervision. If this product, used as directed does not provide relief, discontinue use and consult a doctor.

Directions:

Break front tab first. To unlock, press in special Child Resistant (R) tab in back of the actuator while turning the actuator to the right. Press the actuator down repeatedly until product dispenses to prime spray pump. Apply 3 or more sprays, not to exceed 10, to head and shaft of penis 10 minutes before sexual intercourse, or use as directed by a doctor. Recommended Initial Dosage: 3 sprays. Rub Promescent into the skin of the penis until all of the product is absorbed. Wash product off after intersourse. After spraying, turn actuator to the left to lock.

Inactive Ingredients:

Acrylates/C10-30 Alkyl Acrylate Crosspolymer, Ceteareth-20, Cetearyl Alcohol, Citric Acid, Dimethicone, Farnesol, Fragrance, Glycerin, Hydrogenated Polyisobutene, Macadamia Ternifolia Seed Oil, Panthenol, Phenoxyethanol, Purified Water (Aqua), SD Alcohol 40-B, Sodium Hydroxide, Soy Lecithin, Stearoxytrimethylsilane, Stearyl Alcohol, Thymol, Tocopheryl Acetate (Vitamin E).